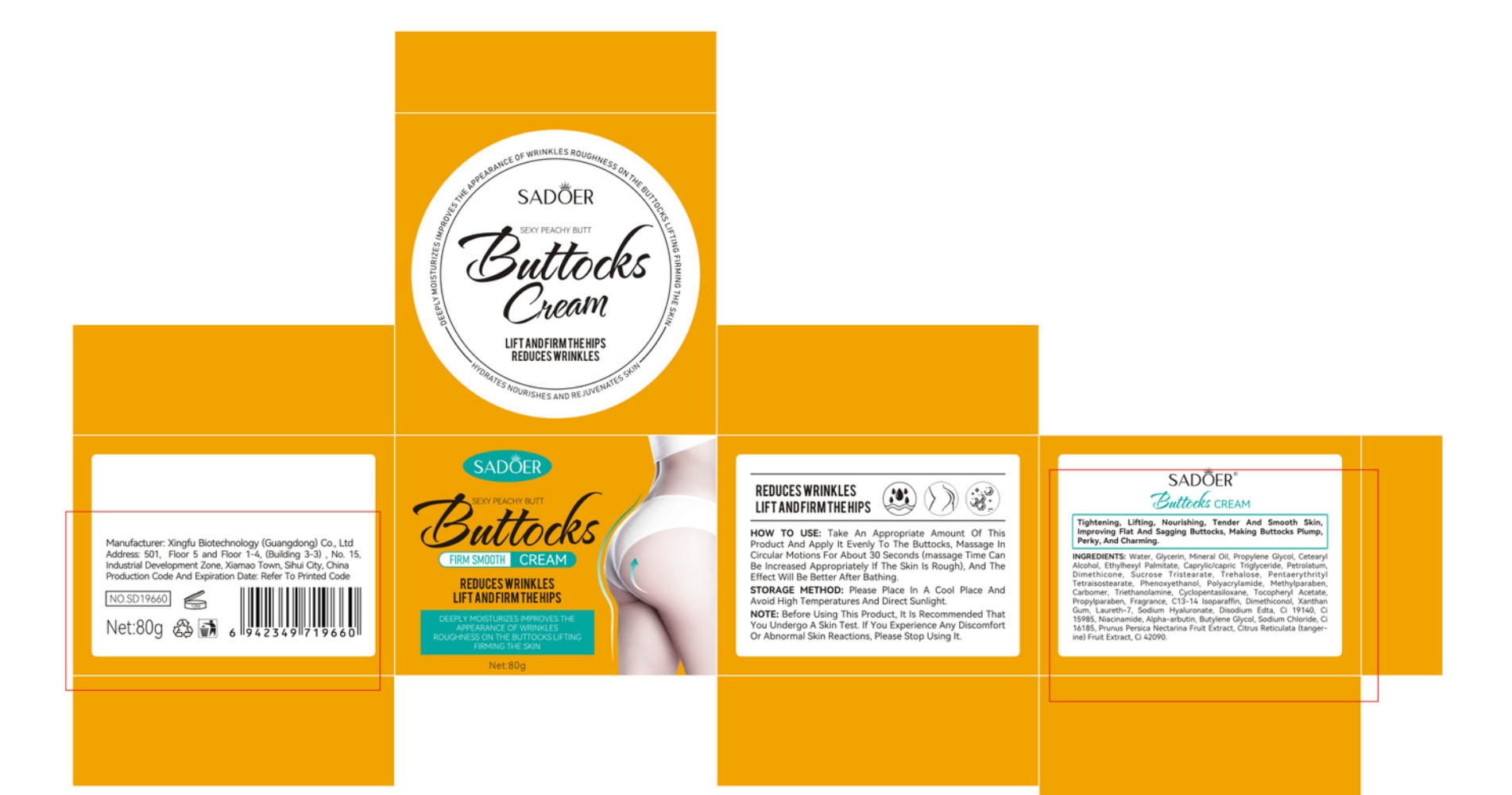 DRUG LABEL: sadoerbuttockscream
NDC: 84372-044 | Form: LOTION
Manufacturer: Shenzhen Zhumeng Times Technology Co., Ltd.
Category: otc | Type: HUMAN OTC DRUG LABEL
Date: 20240904

ACTIVE INGREDIENTS: NIACINAMIDE 5 g/80 g
INACTIVE INGREDIENTS: FD&C YELLOW NO. 5; DIMETHICONE; FD&C BLUE NO. 1; SUCROSE TRISTEARATE; XANTHAN GUM; MINERAL OIL; WATER; GLYCERIN; PROPYLENE GLYCOL DIBUTYRATE; CETOSTEARYL ALCOHOL; MEDIUM-CHAIN TRIGLYCERIDES; DIMETHICONE 6; TREHALOSE; PENTAERYTHRITYL TETRAISOSTEARATE; METHYLPARABEN; CYCLOMETHICONE 5; C13-14 ISOPARAFFIN; FD&C YELLOW NO. 6; ALPHA-ARBUTIN; BUTYLENE GLYCOL; SODIUM CHLORIDE; AMARANTH; PEACH; NECTARINE; CALCIUM CITRATE MALATE; .ALPHA.-TOCOPHEROL ACETATE; PHENOXYETHANOL; PROPYLPARABEN; HYALURONATE SODIUM; EDETATE DISODIUM; PETROLATUM; IVERMECTIN; TROLAMINE; FRAGRANCE 13576; LAURETH-7; ETHYLHEXYL PALMITATE; TANGERINE; POLYACRYLAMIDE (10000 MW)

Active ingredients

niacinamide 5%

Purpose

Tightening,lifting, nourishing,tender and smooth skin, improving flat
and sagging buttocks,making buttocks plump, perky,and charming.

Uses

Take an appropriate amount of this product
and apply it evenly to the buttocks,massage in circular
motions for about 30 seconds(massage time, can be
increased appropriately if the skin is rough),and the effect
will be better after bathing.

Warnings

Before using this product, it is recommended that
you undergo a skin test. If you experience any discomfort
or abnormal skin reactions,please stop using it.

Dosage and administration

For external use only.

Do not use

Before using this product, it is recommended that
you undergo a skin test. If you experience any discomfort
or abnormal skin reactions,please stop using it.

When using section

Take an appropriate amount of this product
and apply it evenly to the buttocks,massage in circular
motions for about 30 seconds(massage time, can be
increased appropriately if the skin is rough),and the effect
will be better after bathing.

stop use

Before using this product, it is recommended that
you undergo a skin test. If you experience any discomfort
or abnormal skin reactions,please stop using it.

Keep out of reach of children.

If sxralowed, get medical help or contact a Poison Conirol Cenler ngiht away.

Inactive ingredients

Water,glycerin,mineraloil,propyleneglycol,cetearylalcohol,ethylhexyl palmitate,caprylic/caprictriglyceride,petrolatum,dimethicone,sucrosetristearate, trehalose,pentaerythrityltetraisostearate, phenoxyethanol,polyacrylamide,methylparaben,carbomer, triethanolamine,cyclopentasiloxane, tocopheryl acetate, propylparaben, fragrance,c13-14 isoparaffin,dimethiconol,xanthan gum,laureth-7, sodium hyaluronate,disodium edta,Cl 19140,Cl 15985, alpha-arbutin, butylene glycol,sodium chloride,cl 16185,prunus persica nectarina fruit extract,citrus reticulata (tangerine) fruit extract,Cl 42090